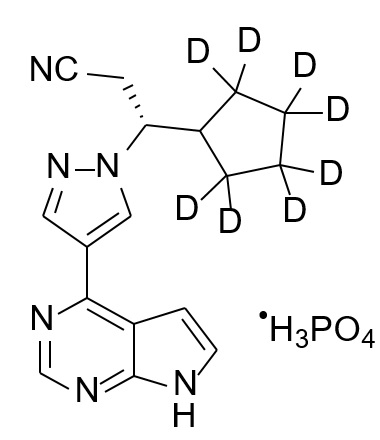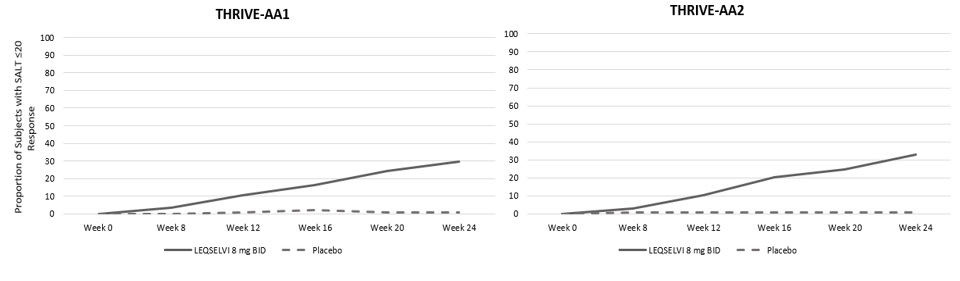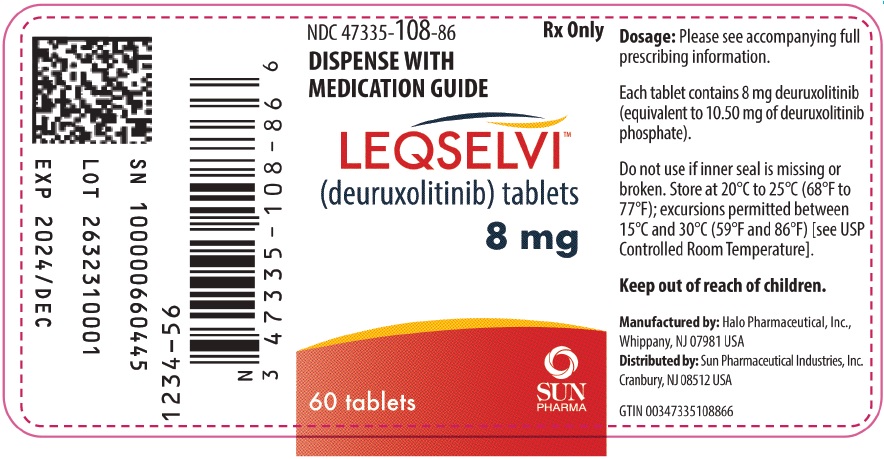 DRUG LABEL: LEQSELVI
NDC: 47335-108 | Form: TABLET, FILM COATED
Manufacturer: Sun Pharmaceutical Industries, Inc.
Category: prescription | Type: HUMAN PRESCRIPTION DRUG LABEL
Date: 20250717

ACTIVE INGREDIENTS: DEURUXOLITINIB PHOSPHATE 8 mg/1 1

HIGHLIGHTS OF PRESCRIBING INFORMATION

These highlights do not include all the information needed to use LEQSELVI safely and effectively. See full prescribing information for LEQSELVI.
LEQSELVI™ (deuruxolitinib) tablets, for oral use
Initial U.S. Approval: 2024

WARNING: SERIOUS INFECTIONS, MORTALITY, MALIGNANCY, MAJOR ADVERSE CARDIOVASCULAR EVENTS, AND THROMBOSIS

WARNING: SERIOUS INFECTIONS, MORTALITY,
MALIGNANCY, MAJOR ADVERSE CARDIOVASCULAR
EVENTS (MACE) and THROMBOSIS

See full prescribing information for complete boxed warning.

- Increased risk of serious bacterial, fungal, viral and opportunistic infections including tuberculosis (TB), that may lead to hospitalization or death. Interrupt treatment with LEQSELVI if a serious infection occurs until the infection is controlled. Test for latent TB before and during therapy; treat latent TB prior to use. Monitor all patients for active TB during treatment, even patients with initial negative, latent TB test. (5.1)
- Higher rate of all-cause mortality, including sudden cardiovascular death with another Janus kinase inhibitor (JAK) vs. TNF blockers in rheumatoid arthritis (RA) patients. LEQSELVI is not approved for use in RA patients. (5.2)
- Malignancies have occurred in patients treated with LEQSELVI. Higher rate of lymphomas and lung cancers with another JAK inhibitor vs. TNF blockers in RA patients. (5.3)
- Higher rate of MACE (defined as cardiovascular death, myocardial infarction, and stroke) with another Janus kinase inhibitor (JAK) vs. TNF blockers in rheumatoid arthritis (RA) patients. (5.4)
- Thrombosis has occurred in patients treated with LEQSELVI. Increased incidence of pulmonary embolism, venous and arterial thrombosis with another JAK inhibitor vs. TNF blockers. (5.5)

1 INDICATIONS AND USAGE

LEQSELVI is a Janus kinase (JAK) inhibitor indicated for the treatment of adults with severe alopecia areata. (1)

Limitations of Use:
LEQSELVI is not recommended for use in combination with other JAK inhibitors, biologic immunomodulators, cyclosporine or other potent immunosuppressants. (1)

2 DOSAGE AND ADMINISTRATION

- For recommended testing, evaluations, and procedures prior to and during LEQSELVI treatment, see Full Prescribing Information. (2.1)
- Recommended dosage is 8 mg twice daily. (2.2)
- For treatment interruption for certain adverse reactions, see Full Prescribing Information. (2.3)

3 DOSAGE FORMS AND STRENGTHS

Tablets: 8 mg. (3)

4 CONTRAINDICATIONS

LEQSELVI is contraindicated in patients:

- Who are CYP2C9 poor metabolizers. (4)
- Using moderate or strong CYP2C9 inhibitors. (4)

5 WARNINGS AND PRECAUTIONS

- Increased Risk of LEQSELVI-Associated Serious Adverse Reactions in CYP2C9 Poor Metabolizers or with Concomitant Use of Moderate or Strong CYP2C9 Inhibitors: LEQSELVI is contraindicated in patients who are CYP2C9 poor metabolizers or patients taking a moderate or strong CYP2C9 inhibitor. (5.6)
- Gastrointestinal Perforations: Monitor patients who may be at increased risk for gastrointestinal perforation. Evaluate promptly patients presenting with new onset abdominal symptoms. (5.7)
- Lipid Elevations, Anemia, Neutropenia, and Lymphopenia: Monitor for changes in lipids, hemoglobin, neutrophils, and lymphocytes. (5.8)
- Immunizations: Avoid use of live vaccines during or immediately prior to LEQSELVI treatment. (5.9)

6 ADVERSE REACTIONS

Most common adverse reactions (≥1%) are: headache, acne, nasopharyngitis, blood creatine phosphokinase increased, hyperlipidemia, fatigue, weight increased, lymphopenia, thrombocytosis, anemia, skin and soft tissue infections, neutropenia, and herpes. (6.1)

To report SUSPECTED ADVERSE REACTIONS, contact Sun Pharmaceutical Industries, Inc. at 1-800-818-4555 or FDA at 1-800-FDA-1088 or www.fda.gov/medwatch.

7 DRUG INTERACTIONS

- Strong CYP3A4 and moderate or strong CYP2C9 inducers: Avoid concomitant use. (7)
- Moderate or strong CYP2C9 inhibitors: Contraindicated. (7)

8 USE IN SPECIFIC POPULATIONS

- Lactation: Breastfeeding is not recommended. (8.2)
- Severe renal impairment: Not recommended. (8.6)
- Severe hepatic impairment: Not recommended. (8.7)

FULL PRESCRIBING INFORMATION

WARNING: SERIOUS INFECTIONS, MORTALITY, MALIGNANCY, MAJOR ADVERSE CARDIOVASCULAR EVENTS, AND THROMBOSIS

- Increased risk of serious bacterial, fungal, viral and opportunistic infections, including tuberculosis (TB), that may lead to hospitalization or death. Interrupt treatment with LEQSELVI if a serious infection occurs until the infection is controlled. LEQSELVI treatment is not recommended in patients with active tuberculosis. Test for latent TB before and during therapy; treat latent TB prior to use. Monitor all patients for active TB during treatment, even patients with initial negative, latent TB test. (5.1)
- Higher rate of all-cause mortality, including sudden cardiovascular death, was observed with another Janus kinase (JAK) inhibitor vs. TNF blockers in rheumatoid arthritis (RA) patients. LEQSELVI is not approved for use in RA patients. (5.2)
- Malignancies were reported in patients treated with LEQSELVI. Higher rate of lymphomas and lung cancers was observed with another JAK inhibitor vs. TNF blockers in RA patients. (5.3)
- Higher rate of major adverse cardiovascular events (MACE) (defined as cardiovascular death, myocardial infarction, and stroke) was observed with another JAK inhibitor vs. TNF blockers in RA patients. (5.4)
- Thrombosis, including cerebral venous sinus thrombosis (CVT), deep vein thrombosis (DVT) and pulmonary embolism (PE) have been reported in patients treated with LEQSELVI. Increased incidence of pulmonary embolism, venous and arterial thrombosis was observed with another JAK inhibitor vs. TNF blockers. (5.5)

1 INDICATIONS AND USAGE

LEQSELVI™ is indicated for the treatment of adult patients with severe alopecia areata.

Limitations of Use

LEQSELVI is not recommended for use in combination with other JAK inhibitors, biologic immunomodulators, cyclosporine, or other potent immunosuppressants.

2 DOSAGE AND ADMINISTRATION

2.1 Recommended Evaluations and Immunizations Prior to and During Treatment

Perform the following prior to treatment with LEQSELVI:

- CYP2C9 genotype determination: Test patients for CYP2C9 variants to determine CYP2C9 genotype. LEQSELVI is contraindicated in patients who are CYP2C9 poor metabolizers (patients with decreased cytochrome P450 (CYP) 2C9 function) [see Contraindications (4)]. An FDA-cleared or -approved test for the detection of CYP2C9 variants to direct the use of LEQSELVI is not currently available.
- Evaluation for use of concomitant CYP2C9 inhibitors: LEQSELVI is contraindicated in patients taking moderate or strong CYP2C9 inhibitors [see Warnings and Precautions (5.6)].
- Active and latent tuberculosis (TB) evaluation: LEQSELVI treatment is not recommended in patients with active TB. For patients with latent TB or those with a negative latent TB test who are at high risk of TB, start preventive therapy for TB prior to LEQSELVI treatment [see Warnings and Precautions (5.1)].
- Viral hepatitis screening in accordance with clinical guidelines: LEQSELVI treatment is not recommended in patients with active hepatitis B or hepatitis C.
- Hepatitis B infection screening: If hepatitis B infection is discovered, follow hepatitis B clinical guidelines, or refer to a liver specialist. Monitor patients for reactivation in accordance with clinical guidelines during treatment [see Warnings and Precautions (5.1)].
- Complete blood count (CBC): LEQSELVI treatment is not recommended in patients with an absolute lymphocyte count (ALC) <500 cells/mm^3 absolute neutrophil count (ANC) <1,000 cells/mm^3, or hemoglobin level <8 g/dl. Monitor complete blood counts periodically during treatment and modify dosage as recommended [see Dosage and Administration (2.3) and Warnings and Precautions (5.8)].
- Complete any necessary immunizations, including herpes zoster vaccinations, according to current immunization guidelines prior to LEQSELVI treatment [see Warnings and Precautions (5.9)].

2.2 Recommended Dosage

The recommended dosage of LEQSELVI for the treatment of severe alopecia areata is 8 mg orally twice daily, with or without food [see Clinical Pharmacology (12.3)].

If a dose is missed, skip the missed dose and resume dosing at the next scheduled dose.

2.3 Treatment Interruption and Resumption

Serious or Opportunistic Infections

If a patient develops a serious or opportunistic infection, interrupt LEQSELVI treatment until the infection is controlled [see Warnings and Precautions (5.1)].

Hematological Abnormalities

Recommendations for LEQSELVI treatment interruption for hematologic abnormalities are described in Table 1 [see Warnings and Precautions (5.8)].

Table 1: Recommendations for LEQSELVI Treatment Interruption for Hematologic Abnormalities and Resumption
Laboratory Measure | Interruption Criterion | Resumption Criterion
Absolute Lymphocyte Count (ALC) | <500 cells/mm^3 | ≥500 cells/mm^3
Absolute Neutrophil Count (ANC) | <1000 cells/mm^3 | ≥1000 cells/mm^3
Hemoglobin | <8 g/dL | ≥8 g/dL

3 DOSAGE FORMS AND STRENGTHS

Tablet: purple, round, debossed with “C” on one side and “8” on the other side

4 CONTRAINDICATIONS

LEQSELVI is contraindicated in patients who:

- Are CYP2C9 poor metabolizers [see Warnings and Precautions (5.6)].
- Are on concomitant moderate or strong CYP2C9 inhibitors [see Warnings and Precautions (5.6)].

5 WARNINGS AND PRECAUTIONS

5.1 Serious Infections

Serious infections have been reported in subjects with alopecia areata receiving LEQSELVI [see Adverse Reactions (6.1)].

Avoid use of LEQSELVI in patients with an active, serious infection including localized infections.

Prior to LEQSELVI treatment, consider the risks and benefits in patients:

- with chronic or recurrent infection
- who have been exposed to tuberculosis
- with a history of a serious or opportunistic infection
- who have resided or traveled in areas of endemic tuberculosis or endemic mycoses; or
- with underlying conditions that may predispose them to infection

Closely monitor patients for the development of signs and symptoms of infection during and after treatment with LEQSELVI. If the patient develops a serious infection, interrupt treatment with LEQSELVI until the infection resolves or is adequately treated. If a patient develops a new infection during treatment with LEQSELVI, initiate complete diagnostic testing appropriate for an immunocompromised patient and appropriate antimicrobial therapy.

Tuberculosis

Evaluate patients for latent and active tuberculosis (TB) infection prior to LEQSELVI treatment. LEQSELVI is not recommended for use in patients with active TB.

Treat patients with latent TB before LEQSELVI treatment. Consider anti-TB therapy prior to LEQSELVI treatment in patients with previously untreated latent TB or active TB in whom an adequate course of treatment cannot be confirmed, and for patients with a negative test for latent TB but who have risk factors for TB infection. Consultation with a physician with expertise in the treatment of TB is recommended to aid in the decision about whether initiating anti-TB therapy is appropriate for an individual patient.

Monitor patients receiving LEQSELVI for signs and symptoms of active TB during treatment, including patients who tested negative for latent TB infection prior to treatment.

Viral Reactivation

Viral reactivation, including cases of herpes virus reactivation (e.g., herpes zoster) were reported in clinical trials with LEQSELVI [see Adverse Reactions (6.1)]. If a patient develops herpes zoster, consider interrupting LEQSELVI treatment until the episode resolves.

The impact of LEQSELVI on chronic viral hepatitis reactivation is unknown. Subjects with positive results for hepatitis B surface antigens (HBsAg), antibodies to hepatitis B core antigens (anti-HBc), or hepatitis C virus (HCV) with detectable HCV RNA at screening were excluded from LEQSELVI clinical trials. Perform screening for viral hepatitis before treatment with LEQSELVI. LEQSELVI is not recommended for use in patients with active hepatitis B or hepatitis C (HCV RNA detected).

If non-active hepatitis B infection is discovered, monitoring for reactivation or prophylactic treatment is recommended. Follow hepatitis B clinical guidelines or refer to a liver specialist. Hepatitis B viral load (HBV-DNA titer) increase, with or without associated elevations in alanine aminotransferase and aspartate aminotransferase, has been reported in subjects with chronic HBV infections receiving JAK inhibitors used to treat inflammatory conditions. The effect of LEQSELVI on viral replication in patients with chronic HBV infection is unknown.

5.2 Mortality

In a large, randomized, postmarketing safety trial of another JAK inhibitor in rheumatoid arthritis (RA) subjects 50 years and older with at least one cardiovascular risk factor, a higher rate of all-cause mortality, including sudden cardiovascular death, was observed in subjects treated with the JAK inhibitor compared with TNF blockers.

Consider the benefits and risks for the individual patient prior to and during treatment with LEQSELVI.

5.3 Malignancy and Lymphoproliferative Disorders

Malignancies were observed in clinical trials of LEQSELVI [see Adverse Reactions 6.1)].

In a large, randomized, postmarketing safety trial of another JAK inhibitor in subjects with RA, a higher rate of malignancies (excluding non-melanoma skin cancer (NMSC)) was observed in subjects treated with the JAK inhibitor compared to those treated with TNF blockers. A higher rate of lymphomas was observed in subjects treated with the JAK inhibitor compared to those treated with TNF blockers. A higher rate of lung cancers was observed in current or past smokers treated with the JAK inhibitor compared to those treated with TNF blockers. In this trial, current or past smokers had an additional increased risk of overall malignancies.

Consider the benefits and risks for the individual patient prior to and during treatment with LEQSELVI, particularly in patients with a known malignancy (other than successfully treated NMSC), patients who develop a malignancy, and patients who are current or past smokers.

Non-melanoma skin cancers

Non-melanoma skin cancers (NMSCs) have been reported in patients treated with LEQSELVI. Periodic skin examination is recommended for patients who are at increased risk for skin cancer.

5.4 Major Adverse Cardiovascular Events (MACE)

In a large, randomized, postmarketing safety trial of another JAK inhibitor in subjects with RA 50 years of age and older with at least one cardiovascular risk factor, a higher rate of major adverse cardiovascular events (MACE) defined as cardiovascular death, non-fatal myocardial infarction (MI), and non-fatal stroke was observed with the JAK inhibitor compared to those treated with TNF blockers. Patients who are current or past smokers are at additional increased risk.

Consider the benefits and risks for the individual patient prior to and during treatment with LEQSELVI, particularly in patients who are current or past smokers and patients with other cardiovascular risk factors. Inform patients about the symptoms of serious cardiovascular events and the steps to take if they occur. Discontinue LEQSELVI in patients that have experienced a myocardial infarction or stroke.

5.5 Thrombosis

Thrombosis, including pulmonary embolism (PE), deep vein thrombosis (DVT) and cerebral venous sinus thrombosis (CVT) have been reported in clinical trials of deuruxolitinib [see Adverse Reactions (6.1)]. There was no clear relationship between platelet count elevations and thrombotic events.

Thrombosis, including DVT, PE, and arterial thrombosis have been reported in subjects receiving JAK inhibitors used to treat inflammatory conditions. Many of these adverse reactions were serious and some resulted in death.

In a large, randomized, postmarketing safety trial of another JAK inhibitor in subjects with RA 50 years of age and older with at least one cardiovascular risk factor, higher rates of overall thrombosis, DVT, and PE were observed compared to those treated with TNF blockers.

Avoid LEQSELVI in patients who may be at increased risk of thrombosis. If symptoms of thrombosis occur, discontinue LEQSELVI and evaluate and treat patients appropriately.

5.6 Increased Risk of LEQSELVI-Associated Serious Adverse Reactions in CYP2C9 Poor Metabolizers or with Concomitant Use of Moderate or Strong CYP2C9 Inhibitors

Higher plasma concentrations of deuruxolitinib, which may increase the risk of LEQSELVI-associated serious adverse reactions such as thrombosis, may occur when LEQSELVI is used in patients who:

- Are CYP2C9 poor metabolizers [see Use in Specific Populations (8.8) and Clinical Pharmacology (12.5)].
- Are on a concomitant moderate or strong CYP2C9 inhibitor [see Drug Interactions (7) and Clinical Pharmacology (12.3)].

Prior to LEQSELVI treatment, test patients for CYP2C9 variants to determine if they are poor metabolizers [see Dosage and Administration (2.1)]. An FDA-cleared or -approved test for the detection of CYP2C9 variants to direct the use of LEQSELVI is not currently available.

LEQSELVI is contraindicated in patients who are CYP2C9 poor metabolizers or patients who are on concomitant moderate or strong CYP2C9 inhibitors [see Contraindications (4)].

5.7 Gastrointestinal Perforations

Gastrointestinal perforations have been reported in clinical trials with LEQSELVI.

Monitor patients treated with LEQSELVI who may be at increased risk for gastrointestinal perforation (e.g., patients with a history of diverticulitis). Evaluate promptly patients presenting with new onset abdominal symptoms for early identification of gastrointestinal perforation.

5.8 Lipid Elevations, Anemia, Neutropenia, and Lymphopenia

Perform a CBC prior to and periodically during treatment with LEQSELVI [see Dosage and Administration (2.1)].

Lipid Elevations

Treatment with LEQSELVI was associated with increases in triglycerides and total cholesterol, including HDL-C and LDL-C [see Adverse Reactions 6.1)]. The effect of these lipid parameter elevations on cardiovascular morbidity and mortality has not been determined. Perform assessment of lipid parameters at baseline and periodically during treatment with LEQSELVI. Manage patients according to clinical guidelines for hyperlipidemia.

Anemia

Treatment with LEQSELVI was associated with an increased incidence of anemia (hemoglobin less than 8 g/dL) compared to placebo [see Adverse Reactions (6.1)]. Avoid or interrupt LEQSELVI treatment in patients with hemoglobin less than 8 g/dL [see Dosage and Administration (2.3)].

Neutropenia

Treatment with LEQSELVI was associated with an increased incidence of neutropenia (ANC less than 1000 cells/mm^3) compared to placebo [see Adverse Reactions (6.1)]. Avoid or interrupt LEQSELVI treatment in patients with an ANC less than 1,000 cells/mm^3 [see Dosage and Administration (2.3)].

Lymphopenia

Treatment with LEQSELVI was associated with an increased incidence of lymphopenia (ALC less than 500 cells/mm^3) compared to placebo [see Adverse Reactions (6.1)]. Avoid or interrupt LEQSELVI treatment in patients with an ALC less than 500 cells/mm^3 [see Dosage and Administration (2.3)].

5.9 Immunizations

Prior to LEQSELVI treatment, complete all necessary immunizations, including varicella zoster or prophylactic herpes zoster vaccinations, in accordance with current immunization guidelines. Avoid use of live vaccines during or immediately prior to LEQSELVI treatment.

6 ADVERSE REACTIONS

The following clinically significant adverse reactions are described elsewhere in the labeling:

- Serious Infections [see Warnings and Precautions (5.1)]
- Malignancy and Lymphoproliferative Disorders [see Warnings and Precautions (5.3)]
- Thrombosis [see Warnings and Precautions (5.5)]
- Gastrointestinal perforations [see Warnings and Precautions (5.7)]
- Lipid Elevations, Anemia, Neutropenia and Lymphopenia [see Warnings and Precautions (5.8)]

6.1 Clinical Trials Experience

Because clinical trials are conducted under widely varying conditions, adverse reaction rates observed in the clinical trials of a drug cannot be directly compared to rates in the clinical trials of another drug and may not reflect the rates observed in practice.

The safety of LEQSELVI was evaluated in three randomized, placebo-controlled clinical trials (including a dose-ranging trial), two open-label trials, and two long-term extension trials in adult subjects with severe alopecia areata. These subjects had at least 50% scalp hair loss as measured by the Severity of Alopecia Tool (SALT) for more than six months. A total of 1,730 subjects with alopecia areata were treated across all trials, representing 1,962.9 patient-years of exposure. There were 974 subjects who were exposed to either LEQSELVI 8 mg or deuruxolitinib 12 mg for at least 1 year and 104 subjects who were exposed for at least 3 years.

Deuruxolitinib 12 mg is not approved.

Among 1,020 subjects enrolled in the placebo-controlled clinical trials, 640 subjects received LEQSELVI 8 mg twice daily, 380 subjects received deuruxolitinib 12 mg twice daily and 299 subjects received placebo twice daily for up to 24 weeks [see Clinical Studies (14)].

Adverse Reactions occurring at ≥1% in the LEQSELVI 8 mg or deuruxolitinib 12 mg twice daily group and at a higher rate than in the placebo group are presented in Table 2. A total of 20 (3.1%) of subjects treated with LEQSELVI 8 mg were discontinued from the trials due to adverse reactions.

Table 2: Adverse Reactions Reported in ≥1% of Subjects with Alopecia Areata Treated with LEQSELVI 8 mg Twice Daily or Deuruxolitinib 12 mg Twice Daily (and More Frequently than Placebo) in Placebo-Controlled Trials Over 24-Weeks
 | Placebo N = 299 n (%)a | LEQSELVI 8 mg twice daily N = 640 n (%)a | Deuruxolitinib 12 mg twice daily N = 380 n (%)a
Acneb | 13 (4.3) | 66 (10.0) | 52 (12.6)
Headache | 30 (9.4) | 83 (12.4) | 44 (10.5)
Nasopharyngitis | 21 (6.7) | 54 (8.1) | 33 (7.7)
Blood creatine phosphokinase increased | 7 (2.2) | 35 (5.3) | 27 (7.4)
Hyperlipidemiac | 10 (3.1) | 30 (4.4) | 19 (5.2)
Fatigued | 12 (3.9) | 26 (3.9) | 20 (4.9)
Skin and soft tissue infectionse | 2 (0.8) | 11 (1.6) | 15 (4.0)
Anemiaf | 3 (1.0) | 18 (2.6) | 16 (3.4)
Weight increased | 4 (1.4) | 19 (2.9) | 10 (2.5)
Neutropeniag | 3 (0.7) | 10 (1.4) | 10 (2.8)
Lymphopenia | 2 (0.6) | 2 (0.3) | 7 (2.0)
Thrombocytosish | 0 | 18 (2.7) | 6 (1.6)
Herpesi | 2 (0.6) | 8 (1.2) | 6 (1.6)
a. %-study size adjusted percentages.
b. Acne includes: acne, dermatitis acneiform, and acne pustular.
c. Hyperlipidemia includes: blood cholesterol increased, low density lipoprotein increased, blood triglycerides increased, hypercholesterolemia, hyperlipidemia, hypertriglyceridemia, and dyslipidaemia.
d. Fatigue includes: fatigue, asthenia, hypersomnia, somnolence, and lethargy.
e. Skin and soft issue infections includes: folliculitis, impetigo, skin infection, subcutaneous abscess, furuncle, paronychia, and pustule.
f. Anemia includes: anemia, hematocrit decreased, hemoglobin decreased, iron deficiency anemia, and red blood cell count decreased.
g. Neutropenia includes: neutropenia and neutrophil count decreased.
h. Thrombocytosis includes: thrombocytosis and platelet count increased.
i. Herpes includes: oral herpes, herpes simplex, genital herpes simplex, and nasal herpes.

Additional adverse drug reactions occurring in fewer than 1% of subjects: herpes zoster, lipase increased, and candidiasis.

A total of 868 subjects in the long-term extension trials received treatment with LEQSELVI 8 mg twice daily and 991 subjects received treatment with deuruxolitinib 12 mg twice daily for 52 weeks. In two open-label extension trials up to 3 years, 829 subjects received treatment with LEQSELVI 8 mg twice daily, and 1066 subjects received treatment with deuruxolitinib 12 mg twice daily.

Specific Adverse Reactions (0-52 weeks)

All Infections

During the 24-week treatment period, infections were reported in 97 subjects (88.0 per 100 patient-years) treated with placebo, 222 subjects (101.5 per 100 patient-years) treated with LEQSELVI 8 mg twice daily and 153 subjects (117.0 per 100 patient years) treated with deuruxolitinib 12 mg twice daily. During the 0-52 week period, infections were reported in 435 subjects (95.5 per 100 patient-years) treated with LEQSELVI 8 mg twice daily and 408 subjects (74.1 per 100 patient-years) treated with deuruxolitinib 12 mg twice daily.

Serious Infections

During the 24-week treatment period, serious infections were reported in 1 subject (0.8 per 100 patient-years) treated with placebo, 5 subjects (1.8 per 100 patient-years) treated with LEQSELVI 8 mg twice daily and 2 subjects (1.2 per 100 patient-years) treated with deuruxolitinib 12 mg twice daily. During the 0-52 week period, serious infections were reported in 5 subjects (0.7 per 100 patient-years) treated with LEQSELVI 8 mg twice daily and 4 subjects (0.5 per 100 patient-years) treated with deuruxolitinib 12 mg twice daily.

Herpes Zoster

During the 24-week treatment period, opportunistic infections (herpes zoster) were reported in 0 subjects treated with placebo, 3 subjects (1.1 per 100 patient-years) treated with LEQSELVI 8 mg twice daily and 3 subjects (1.8 per 100 patient-years) treated with deuruxolitinib 12 mg twice daily. During the 0-52 week period, herpes zoster was reported in 10 subjects (1.5 per 100 patient-years) treated with LEQSELVI 8 mg twice daily and 15 subjects (1.9 per 100 patient-years) treated with deuruxolitinib 12 mg twice daily.

Malignancies

During the 0-52 week period, malignancy excluding NMSC was reported in 3 subjects (0.4 per 100 patient-years) treated with LEQSELVI 8 mg twice daily and 4 subjects (0.5 per 100 patient-years) treated with deuruxolitinib 12 mg twice daily.

Thrombosis

During the 0-52 week period, thrombosis was reported in 0 subjects treated with LEQSELVI 8 mg twice daily and 1 subject (0.1 per 100 patient-years) treated with deuruxolitinib 12 mg twice daily who developed bilateral pulmonary embolism.

Laboratory Abnormalities

Anemia

During the 24-week treatment period, anemia was reported in 3 subjects (2.3 per 100 patient-years) treated with placebo, 19 subjects (6.9 per 100 patient-years) treated with LEQSELVI 8 mg twice daily and 16 subjects (9.6 per 100 patient-years) treated with deuruxolitinib 12 mg twice daily. During the 0-52 week period, anemia was reported in 17 subjects (2.6 per 100 patient-years) treated with LEQSELVI 8 mg twice daily and 38 subjects (5.0 per 100 patient-years) treated with deuruxolitinib 12 mg twice daily.

Neutropenia

During the 24-week treatment period, neutropenia was reported in 3 subjects (2.3 per 100 patient-years) treated with placebo, 10 subjects (3.6 per 100 patient-years) treated with LEQSELVI 8 mg twice daily and 10 subjects (6.0 per 100 patient-years) treated with deuruxolitinib 12 mg twice daily. During the 0-52 week period, neutropenia was reported in 11 subjects (1.6 per 100 patient-years) treated with LEQSELVI 8 mg twice daily and 15 subjects (1.9 per 100 patient-years) treated with deuruxolitinib 12 mg twice daily.

Lymphopenia

During the 24-week treatment period, lymphopenia was reported in 2 subjects (1.5 per 100 patient-years) treated with placebo, 2 subjects (0.7 per 100 patient-years) treated with LEQSELVI 8 mg twice daily and 7 subjects (4.2 per 100 patient-years) treated with deuruxolitinib 12 mg twice daily. During the 0-52 week period, lymphopenia was reported in 4 subjects (0.6 per 100 patient-years) treated with LEQSELVI 8 mg twice daily and 10 subjects (1.3 per 100 patient-years) treated with deuruxolitinib 12 mg twice daily.

Lipid Elevations

During the 24-week treatment period, lipid elevations were reported in 10 subjects (7.7 per 100 patient-years) treated with placebo, 30 subjects (11.0 per 100 patient-years) treated with LEQSELVI 8 mg twice daily and 18 subjects (10.9 per 100 patient-years) treated with deuruxolitinib 12 mg twice daily. During the 0-52 week period, lipid elevations were reported in 47 subjects (7.2 per 100 patient-years) treated with LEQSELVI 8 mg twice daily and 66 subjects (8.7 per 100 patient-years) treated with deuruxolitinib 12 mg twice daily.

Creatine Phosphokinase (CPK) Elevations

During the 24-week treatment period, CPK elevations were reported in 7 subjects (5.4 per 100 patient-years) treated with placebo, 35 subjects (12.9 per 100 patient-years) treated with LEQSELVI 8 mg twice daily and 27 subjects (16.6 per 100 patient-years) treated with deuruxolitinib 12 mg twice daily. During the 0-52 week period, CPK elevations were reported in 49 subjects (7.6 per 100 patient-years) treated with LEQSELVI 8 mg twice daily and 46 subjects (6.1 per 100 patient-years) treated with deuruxolitinib 12 mg twice daily.

Thrombocytosis

During the 24-week treatment period, an increase in platelet count was reported in 0 subjects treated with placebo, 18 subjects (6.6 per 100 patient-years) treated with LEQSELVI 8 mg twice daily and 6 subjects (3.6 per 100 patient-years) treated with deuruxolitinib 12 mg twice daily.

During the 0-52 week period, an increase in platelet count was reported in 20 subjects (3.0 per 100 patient-years) treated with LEQSELVI 8 mg twice daily and 26 subjects (3.4 per 100 patient-years) treated with deuruxolitinib 12 mg twice daily.

Adverse Reactions Observed after 52 weeks

Thrombosis

Venous thromboembolic events were reported in 4 subjects treated with deuruxolitinib 12 mg twice daily between Week 52 and Week 98. These 4 subjects experienced 7 thrombotic events (0.2 per 100 patient-years), including deep vein thrombosis (DVT), bilateral pulmonary embolism (PE), pulmonary embolism, and cerebral venous sinus thrombosis (CVT).

7 DRUG INTERACTIONS

Effect of Other Drugs on LEQSELVI

Strong CYP3A and moderate or strong CYP2C9 inducers:

Avoid concomitant use of LEQSELVI with strong CYP3A and moderate or strong CYP2C9 inducers.

Deuruxolitinib is a CYP2C9 and CYP3A substrate. Concomitant use with a strong CYP3A and moderate or strong CYP2C9 inducer decreases deuruxolitinib exposure (Cmax and AUC), which may reduce LEQSELVI efficacy [see Clinical Pharmacology (12.3)].

Moderate or strong CYP2C9 inhibitors:

LEQSELVI is contraindicated in patients taking moderate or strong CYP2C9 inhibitors [see Contraindications (4)].

Deuruxolitinib is a CYP2C9 substrate. Concomitant use with a moderate or strong CYP2C9 inhibitor is estimated to increase deuruxolitinib exposure (Cmax and AUC), which may increase the risk of LEQSELVI serious adverse reactions such as thrombosis [see Clinical Pharmacology (12.3)].

8 USE IN SPECIFIC POPULATIONS

8.1 Pregnancy

Risk Summary

Based on the findings from animal reproduction studies, deuruxolitinib may cause fetal harm during pregnancy. Available data from pregnancies reported in clinical trials with LEQSELVI are not sufficient to evaluate for a drug-associated risk for major birth defects, miscarriage, or adverse maternal or fetal outcomes. In animal reproduction studies, oral administration of deuruxolitinib to pregnant rats during the period of organogenesis at a dose 4.8 times the maximum recommended human dose (MRHD) resulted in reduced fetal weight and increased skeletal malformation. Oral administration of deuruxolitinib to pregnant rabbits during the period of organogenesis at a dose 0.3 times the MRHD resulted in maternal toxicity, reduced fetal weight, and increased post-implantation loss. Oral administration of deuruxolitinib to pregnant rats during pregnancy and lactation periods at a dose 5 times the MRHD resulted in maternal toxicity, decreased pup survival, and adverse effects on postnatal development (see Data). Advise pregnant women of the potential risk to a fetus.

The background risks of major birth defects and miscarriage for the indicated population are unknown. All pregnancies carry some risk of birth defects, loss, or other adverse outcomes. In the U.S. general population, the estimated background risk of major birth defects is 2 to 4% of the general population and miscarriage occurs in 15 to 20% of clinically recognized pregnancies.

Data

Animal Data

In an embryo-fetal development study, deuruxolitinib was administered to pregnant rats during the period of organogenesis at oral doses of 15, 30, and 60 mg/kg/day. Reduced fetal weight and increased fetal skeletal malformation were noted at 60 mg/kg/day (4.8 times the MRHD based on AUC comparison) with no maternal toxicity. No embryo-fetal toxicity was observed at doses up to 30 mg/kg/day (equivalent to MRHD based on AUC comparison). In another embryo-fetal development study, deuruxolitinib was administered to pregnant rabbits during the period of organogenesis at oral doses of 6, 30, and 60 mg/kg/day. Reduced fetal weight and increased post-implantation loss were noted at 60 mg/kg/day (0.3 times the MRHD based on AUC comparison), at which maternal toxicity was observed. No embryo-fetal toxicity was noted at doses up to 30 mg/kg/day (0.05 times the MRHD based on AUC comparison).

In a pre- and postnatal development study in rats, deuruxolitinib was administered to pregnant rats during pregnancy and lactation periods at oral doses of 15, 30, and 75 mg/kg/day. Decreases in liveborn pups and pup survival, decreased pup activity and lower pup body weights, and adverse effects on reproductive outcome in the second generation females (decreased corpora lutea, implantation, and number of live embryos, and increased resorption and post-implantation loss) were noted at 75 mg/kg/day (5 times the MRHD based on AUC comparison), at which maternal toxicity was also observed. No adverse effects on pre- and postnatal development were noted at doses up to 30 mg/kg/day (0.8 times the MRHD based on AUC comparison).

8.2 Lactation

Risk Summary

There are no data on the presence of deuruxolitinib in human milk, the effects on the breast-fed infant, or the effects on milk production. Deuruxolitinib was present in the milk of lactating rats (see Data). When a drug is present in animal milk, it is likely that the drug will be present in human milk. Because of the potential for serious adverse reactions in nursing infants, advise women not to breastfeed during treatment with LEQSELVI and for one day after the last dose (approximately 5 to 6 elimination half-lives).

Data

Animal Data

Following a single oral dose of 10 mg/kg administered to lactating rats on lactation day 14, deuruxolitinib concentrations were up to 20 times higher in milk than in plasma.

8.3 Females and Males of Reproductive Potential

Contraception

Females

Based on animal studies, deuruxolitinib may cause fetal harm when administered during pregnancy [see Use in Specific Populations (8.1)]. Consider pregnancy planning and prevention for females of reproductive potential.

8.4 Pediatric Use

The safety and effectiveness of LEQSELVI have not been established in pediatric patients.

8.5 Geriatric Use

Of the 600 subjects treated with LEQSELVI 8 mg in phase 3 clinical trials, 2 (0.3%) were 65 years of age or older. Clinical trials of LEQSELVI did not include sufficient numbers of subjects 65 years of age and older to determine whether they respond differently from younger adult subjects.

8.6 Renal Impairment

LEQSELVI is not recommended for use in patients with severe renal impairment or end-stage renal disease (eGFR < 30 ml/min). No adjustment of dosage is required in patients with mild or moderate renal impairment.

The effect of severe renal impairment on deuruxolitinib pharmacokinetics is unknown [see Clinical Pharmacology (12.3)].

8.7 Hepatic Impairment

LEQSELVI is not recommended for use in patients with severe hepatic impairment (Child Pugh C). No adjustment of dosage is required in patients with mild (Child Pugh A) or moderate (Child Pugh B) hepatic impairment.

The effect of severe hepatic impairment on deuruxolitinib pharmacokinetics is unknown [see Clinical Pharmacology (12.3)].

8.8 CYP2C9 Poor Metabolizers

Based on modeling, higher exposure of deuruxolitinib in patients who are CYP2C9 poor metabolizers is expected with concomitant use of LEQSELVI, which may increase the risk of LEQSELVI-associated serious adverse reactions. Before initiation of treatment with LEQSELVI, test patients to determine CYP2C9 genotype. An FDA-cleared or -approved test for the detection of CYP2C9 variants to direct the use of LEQSELVI is not currently available [see Warnings and Precautions (5.6) and Clinical Pharmacology (12.5)].

10 OVERDOSAGE

There is no experience regarding human overdose with LEQSELVI.

There is no specific antidote for overdose with LEQSELVI. Treatment should be symptomatic and supportive and monitor patients for signs and symptoms of adverse reactions [see Adverse Reactions (6.1)].

In case of overdose, consider contacting the Poison Center at 1-800-222-1222 for latest recommendations.

11 DESCRIPTION

LEQSELVI (deuruxolitinib) tablets contain the phosphate salt of deuruxolitinib, a Janus kinase (JAK) inhibitor, for oral administration.

Deuruxolitinib phosphate is a white to off-white crystalline solid with the chemical name 1H-Pyrazole-1-propanenitrile, β-(cyclopentyl-2,2,3,3,4,4,5,5-d8)-4-(7H-pyrrolo[2,3-d]pyrimidin-4-yl)-, (βR)-, phosphate (1:1).

Deuruxolitinib has high aqueous solubility at low pH. Deuruxolitinib phosphate has a molecular weight of 412.42 g/mol and a molecular formula of C17H13D8N6O4P. The structural formula is:

Each tablet contains 8 mg of deuruxolitinib (equivalent to 10.50 mg of deuruxolitinib phosphate) and the following excipients: colloidal silicon dioxide, lactose monohydrate, low-substituted hydroxypropyl cellulose, magnesium stearate, microcrystalline cellulose and povidone. The tablet film coating contains the following excipients: carmine, FD&C blue #2 aluminum lake, glyceryl mono and dicaprylocaprate, polyvinyl alcohol, sodium lauryl sulfate, talc, and titanium dioxide.

12 CLINICAL PHARMACOLOGY

12.1 Mechanism of Action

Deuruxolitinib is a Janus kinase (JAK) inhibitor. JAKs mediate the signaling of a number of cytokines and growth factors that are important for hematopoiesis and immune function. JAK signaling involves recruitment of STATs (signal transducers and activators of transcription) to cytokine receptors, activation and subsequent localization of STATs to the nucleus leading to modulation of gene expression.

In an in vitro kinase activity assay, deuruxolitinib had greater inhibitory potency for JAK1, JAK2 and TYK2 relative to JAK3. The relevance of inhibition of JAK enzymes to therapeutic effectiveness is not currently known.

12.2 Pharmacodynamics

Deuruxolitinib Inhibition of IL-6 Induced STAT3 Phosphorylation

Deuruxolitinib inhibited whole blood IL-6 stimulated pSTAT3 in healthy subjects 2 hours post-dose. The relevance of this finding in patients is unknown.

Cardiac Electrophysiology

At concentrations approximately 4-fold higher than the Cmax associated with the highest dose evaluated clinically, 12 mg twice-daily, deuruxolitinib does not prolong the QT interval to any clinically relevant extent.

12.3 Pharmacokinetics

Following oral administration of deuruxolitinib, Cmax and AUCs increased dose proportionally over a dose range from 8 mg to 48 mg (6 times the approved recommended dosage) in healthy subjects. Steady-state plasma concentrations were achieved within 1 to 2 days, with minimal accumulation, after twice daily administration.

Absorption

Deuruxolitinib bioavailability is 90%, with peak plasma concentrations reached within 1.5 hrs.

Effect of Food

No clinically significant differences in the pharmacokinetics of deuruxolitinib were observed following administration of a high fat, high calorie meal (approximately 50% fat and 800-1000 calories).

Distribution

The deuruxolitinib steady state volume of distribution is approximately 50L. Deuruxolitinib plasma protein binding is 91.5% and blood to plasma concentration ratio is approximately 1.3.

Elimination

The deuruxolitinib mean elimination half-life is approximately 4 hrs.

Metabolism

Deuruxolitinib is primarily metabolized by CYP2C9 (76%) and CYP3A4 (21%) and to a lesser extent by CYP1A2 (3%). The two most abundant human metabolites C-21714 and C-21717, each of which accounted for approximately 5% of total drug-related AUC and both are approximately 10-fold less pharmacologically active than deuruxolitinib.

Excretion

After a single dose of radiolabeled deuruxolitinib, there was no unchanged dose recovered in either urine or feces.

Specific Populations

No clinically significant differences in the pharmacokinetics of deuruxolitinib were observed based on race [White (75%), African American (17%) and Asian (6%)], ethnicity [Hispanic or Latino (12%)], age (18-65 years), body weight (40.4-173 kg), mild to moderate renal impairment (eGFR 30-89 mL/min, MDRD), or mild to moderate hepatic impairment (Child Pugh A or B). The effect of severe renal impairment (eGFR < 30 mL/min, MDRD) or severe hepatic impairment (Child Pugh C) on deuruxolitinib pharmacokinetics is unknown.

Drug Interaction Studies

Clinical Studies and Model-Informed Approaches

Effect of Other Drugs on LEQSELVI

Strong CYP3A4 and Moderate or strong CYP2C9 Inducers: Deuruxolitinib AUC decreased by 78% and Cmax by 41% following concomitant use of multiple doses of 600 mg rifampin (strong CYP3A4 and moderate CYP2C9 inducer) with a single dose of 12 mg deuruxolitinib (1.5 times the approved 8 mg dose).

Strong CYP2C9 Inhibitors: Based on modeling, deuruxolitinib AUC is predicted to be increased by 200% and Cmax by 25% following concomitant use of multiple dosages of a strong CYP2C9 inhibitor with a single dose of 12 mg deuruxolitinib (1.5 times the approved 8 mg dose).

Moderate CYP2C9 Inhibitors: Deuruxolitinib AUC increased by 140% and Cmax by 21% following concomitant use of multiple dosages of 200 mg fluconazole (dual moderate CYP3A4 and CYP2C9 inhibitor) with a single dose of 12 mg deuruxolitinib (1.5 times the approved 8 mg dose).

Other Drugs: No clinically significant differences in deuruxolitinib pharmacokinetics were observed when used concomitantly with itraconazole (strong CYP3A4 inhibitor) or are expected with efavirenz (moderate CYP3A4 inducer).

Effect of LEQSELVI on Other Drugs:

No clinically significant differences in the pharmacokinetics of the following drugs were observed when co-administered with deuruxolitinib: midazolam (a sensitive CYP3A4 substrate), oral contraceptives (ethinyl estradiol and levonorgestrel).

In Vitro Studies

Cytochrome P450 (CYP) Enzymes: Deuruxolitinib is not an inhibitor of CYP1A2, CYP2B6, CYP2C8, CYP2C19, CYP2D6, or CYP3A4. Deuruxolitinib is not an inducer of CYP1A2 or CYP2B6, CYP2C8 or CYP2C19.

Transporter Systems: Deuruxolitinib is a substrate of BCRP and MDR1 but not a substrate of the uptake transporters OATP1B1 and OATP1B3. Deuruxolitinib is not an inhibitor of OATP1B1, OATP1B3 and OCT1 but is an inhibitor of BCRP, BSEP, OAT3 and MATE2-K.

12.5 Pharmacogenomics

Deuruxolitinib is primarily metabolized by CYP2C9 (76%) and CYP3A4 (21%). CYP2C9 activity is reduced in patients with genetic variants in CYP2C9, such as the CYP2C9∗2 and CYP2C9∗3 alleles. The impact of CYP2C9 genetic variants on the pharmacokinetics of deuruxolitinib has not been directly evaluated. Based on drug-drug interaction modeling data, CYP2C9 poor metabolizers (e.g., ∗2/∗3, ∗3/∗3) may have up to 2-fold higher concentrations of deuruxolitinib, when compared to normal metabolizers [see Warnings and Precautions (5.6)].

The pharmacokinetics of deuruxolitinib were not evaluated in individuals who are intermediate metabolizers (e.g., individuals with ∗1/∗3 genotype).

The prevalence of the CYP2C9 poor metabolizer phenotype is approximately 2 to 3% in White populations, 0.5 to 4% in Asian populations, and <1% in Black or African American populations. Other decreased or nonfunctional CYP2C9 alleles (e.g., ∗5, ∗6, ∗8, ∗11) are more prevalent in Black or African American populations.

13 NONCLINICAL TOXICOLOGY

13.1 Carcinogenesis, Mutagenesis, Impairment of Fertility

Deuruxolitinib was not carcinogenic when administered orally in a 6-month transgenic rasH2 mouse study at doses up to 100 mg/kg/day. In a 2-year rat carcinogenicity study, no drug-related tumors were observed at oral doses of deuruxolitinib up to 30 mg/kg/day (0.6 times the MRHD based on AUC comparison).

Deuruxolitinib was positive in an in vitro micronucleus assay, but negative in a bacterial mutation assay (the Ames test), an in vitro chromosome aberration assay and an in vivo rat micronucleus assay.

In fertility and early embryonic development studies in rats, deuruxolitinib was administered to male rats prior to mating to conception, or to female rats prior to mating, through conception, to gestation day 7. Deuruxolitinib had no adverse effects on male or female fertility at oral doses up to 100 mg/kg/day (2.2 times MRHD in males and 14 times MRHD in females based on AUC comparison). However, adverse effects on early embryonic development were noted, including decreased viable embryos and increased pre-implantation loss observed at doses ≥ 30 mg/kg/day (0.9 times MRHD based on AUC comparison), and increased post-implantation loss and resorption at 100 mg/kg/day (14 times MRHD based on AUC comparison). No adverse effects on early embryonic development were observed at 10 mg/kg/day (0.2 times MRHD based on AUC comparison).

14 CLINICAL STUDIES

Two multicenter, randomized, double-blind, placebo-controlled phase 3 clinical trials (AA-1 [NCT04518995] and AA-2 [NCT04797650]), evaluated a total of 1,209 adult subjects with alopecia areata (AA), who had at least 50% scalp hair loss as measured by the Severity of Alopecia Tool (SALT) for more than six months. In both trials, subjects received LEQSELVI 8 mg twice daily, deuruxolitinib 12 mg twice daily, or placebo twice daily for 24 weeks.

Deuruxolitinib 12 mg is not approved.

The trial population ranged from 18 to 65 years of age. Among the subjects enrolled, 64% were female, 74% were White, 9% were Black or African American, and 6% were Asian; 8% identified as Hispanic or Latino. At baseline, subjects had average current episode of hair loss of approximately 4 years, with 59% of subjects having complete or near complete scalp hair loss (defined as ≥ 95% scalp hair loss). The mean pooled baseline SALT scores across treatment groups ranged from 85.9 to 88.6 with a mean duration of current episode of hair loss of ranging 3.7 to 3.9 years. Approximately 73% of subjects had eyebrow hair involvement and 70% of subjects had eyelash hair involvement.

The primary endpoint for both trials assessed the proportion of subjects who achieved at least 80% scalp hair coverage (SALT score of ≤ 20) at Week 24. Key secondary outcomes included the percentage of responders (defined as “satisfied” or “very satisfied”) at Week 24 on the Satisfaction of Hair Patient-Reported Outcome (SPRO) and the percentage of subjects achieving an absolute SALT score of ≤ 20 at Week 20, 16, 12, and 8.

Upon completion of the 24-week trials, subjects were eligible to enroll in a long-term extension trial.

Clinical Response

Assessment of scalp hair loss was based on the SALT score. At Week 24, a greater proportion of subjects had a SALT ≤ 20 response (80% or more scalp hair) and SALT ≤ 10 response (90% or more scalp hair) with LEQSELVI 8 mg twice daily compared to placebo (Table 3).

Table 3: Clinical Response at Week 24 in Adult Subjects with Severe AA in Trials AA-1 and AA-2
 | Trial AA-1 |  | Trial AA-2
 | Placebo (N=140) | LEQSELVI 8 mg twice daily (N=351) | Placebo (N=127) | LEQSELVI 8 mg twice daily (N=249)
SALT scores ≤ 20 Common risk difference from Placebo (95% CI) | 1% | 29% 28% (23%, 33%) | 1% | 32% 31% (25%, 37%)
SALT scores ≤ 10 Common risk difference from Placebo (95% CI) | 0%a | 20% 21% (16%, 25%)a | 0%a | 24% 24% (19%, 30%)a
a Not adjusted for multiplicity.

Table 4: Evaluation of Patient Satisfaction with Scalp Hair Coverage at Weeks 24 in Adult Subjects with Severe AA in Trials AA-1 and AA-2
 | Trial AA-1 |  | Trial AA-2
 | Placebo (N=140) | LEQSELVI 8 mg twice daily (N=351) | Placebo (N=127) | LEQSELVI 8 mg twice daily (N=249)
“Very Satisfied”a | 2% | 19% | 0% | 18%
“Satisfied”a | 3% | 23% | 2% | 28%
“Neither Satisfied nor Dissatisfied” | 16% | 19% | 13% | 15%
“Dissatisfied” | 25% | 18% | 18% | 16%
“Very Dissatisfied” | 54% | 21% | 67% | 23%
a In Trial AA-1, the proportion of responders (defined as subjects who were “satisfied” or “very satisfied”) on LEQSELVI was 42% compared to 5% on placebo. In Trial AA-2, the proportion of responders on LEQSELVI was 46% compared to 2% on placebo.

Figure 1: Clinical Response over Time in Adult Subjects with Severe AA in Trials AA- 1 and AA-2

The efficacy of LEQSELVI was generally comparable across multiple subgroups including age, gender, and body weight among these subgroups. The results for SALT score ≤ 20 at Week 24 by baseline scalp hair loss severity are presented in Table 5.

Table 5: Adult Subjects with Severe AA with Absolute SALT Scores ≤ 20 at Week 24 by Baseline Scalp Hair Loss Severity in Trials AA-1 and AA-2
 | Trials AA-1 and AA-2
 | Placebo | LEQSELVI 8 mg BID
50% to 94% Scalp Hair Loss
N SALT ≤ 20 | 110 2% | 248 46%
95% to 100% Scalp Hair Loss
N SALT ≤ 20 | 157 0% | 352 20%
BID = twice-daily

16 HOW SUPPLIED/STORAGE AND HANDLING

How Supplied:

LEQSELVI tablets are packaged in white, high-density polyethylene (HDPE) bottles and closed with 24 mm white child-resistant caps with foil liner. Each bottle contains 1 g silica-gel canister. LEQSELVI is available as purple, round, immediate-release tablets debossed with “C” on one side and “8” on the other side:

- 8 mg: 60 tablets in a bottle; NDC: 47335-108-86

Storage and Handling:

Store at 20°C to 25°C (68°F to 77°F); excursions permitted between 15°C and 30°C (59°F and 86°F) [see USP Controlled Room Temperature].

Store in the original bottle to protect from moisture.

17 PATIENT COUNSELING INFORMATION

Advise the patient to read the FDA-approved patient labeling (Medication Guide)

Serious Infections

Advise patients that they are more likely to develop infections when taking LEQSELVI.

Advise patients that the risk of herpes zoster is increased in patients treated with LEQSELVI and some cases can be serious [see Warnings and Precautions (5.1)].

Instruct patients to tell their healthcare provider if they develop any signs or symptoms of an infection [see Warnings and Precautions (5.1)].

Malignancies and Lymphoproliferative Disorders

Inform patients that LEQSELVI may increase the risk of developing certain cancers, including skin cancers, and that periodic skin examinations should be performed while using LEQSELVI. Instruct patients to inform their healthcare provider if they have ever had any type of cancer [see Warnings and Precautions (5.3)].

Major Adverse Cardiovascular Events

Inform patients that LEQSELVI may increase the risk of major adverse cardiovascular events (MACE) including myocardial infarction, stroke, and cardiovascular death. Instruct all patients, especially current or past smokers or patients with other cardiovascular risk factors, to be alert for the development of signs and symptoms of cardiovascular events [see Warnings and Precautions (5.4)].

Thrombosis

Advise patients that events of DVT, PE and CVT have been reported in clinical trials with LEQSELVI. Instruct patients to seek immediate medical attention if they develop any signs or symptoms of a DVT, PE, or CVT [see Warnings and Precautions (5.5)].

Increased Risk of LEQSELVI-Associated Serious Adverse Reactions in CYP2C9 Poor Metabolizers or with Concomitant Use of Moderate or Strong CYP2C9 Inhibitors

Advise patients to inform their healthcare providers of all medications they are taking, including prescription medicines, over-the-counter drugs, vitamins, and herbal products (e.g., St. John's wort) [see Warnings and Precautions (5.6)].

Gastrointestinal Perforations

Inform patients that gastrointestinal perforations have been reported in clinical trials with LEQSELVI. Instruct patients to seek medical care immediately if they experience new onset of abdominal pain, fever, chills, nausea, or vomiting [see Warnings and Precautions (5.7)].

Laboratory Abnormalities

Inform patients that LEQSELVI may affect certain lab tests, and that blood tests are required before and during LEQSELVI treatment [see Warnings and Precautions (5.8)].

Immunizations

Advise patients that vaccination with live vaccines is not recommended during or immediately prior to LEQSELVI treatment. Instruct patients to inform their healthcare practitioner that they are taking LEQSELVI prior to a potential vaccination [see Warnings and Precautions (5.9)].

Pregnancy

Advise pregnant patients and patients of reproductive potential of the potential risk to a fetus and to inform their healthcare provider if they are pregnant or plan to become pregnant during treatment with LEQSELVI. Inform patients to report their pregnancy to Sun Pharmaceutical Industries, Inc at 1-800-818-4555 [see Use in Specific Populations (8.1) and (8.3)].

Lactation

Advise patients not to breastfeed during treatment with LEQSELVI and for one day after the last dose [see Use in Specific Populations (8.2)].

Manufactured for Sun Pharmaceutical Industries, Inc by: Halo Pharmaceutical, Inc, Whippany, NJ, 07981, USA

U.S. Patent No. 10,561,659; 10,265,258; 11,298,570 and 11,919,907

LEQSELVI is a trademark of Sun Pharmaceutical Industries, Inc.

© 2024 Sun Pharmaceutical Industries, Inc. All rights reserved

Code# 2142-00

7/2024

PATIENT INFORMATION

MEDICATION GUIDE

LEQSELVI™ [lek-sel-vee]
(deuruxolitinib)
tablets, for oral use

What is the most important information I should know about LEQSELVI?
LEQSELVI may cause serious side effects, including:

1. Serious Infections. LEQSELVI is a medicine that affects your immune system. LEQSELVI can lower the ability of your immune system to fight infections. Some people have had serious infections during treatment with LEQSELVI, caused by bacteria, fungi or viruses that can spread throughout the body. Some people may die from these infections.

- Your healthcare provider should test you for TB before starting treatment with LEQSELVI.
- Your healthcare provider should watch you closely for signs and symptoms of TB during treatment with LEQSELVI.

You should not start taking LEQSELVI if you have any kind of infection unless your healthcare provider tells you it is okay. You may be at a higher risk of developing shingles (herpes zoster).

Before starting LEQSELVI, tell your healthcare provider if you:

- are being treated for an infection.
- have an infection that does not go away or that keeps coming back.
- have diabetes, chronic lung disease, HIV, or a weak immune system. People with these conditions have a higher chance for infections.
- have TB or have been in close contact with someone with TB.
- have had shingles (herpes zoster).
- have had hepatitis B or hepatitis C.
- live, or have lived, or have traveled to certain parts of the country (such as Ohio and Mississippi River valleys and the Southwest) where there is an increased chance for getting certain kinds of fungal infections. These infections may happen or become more severe if you use LEQSELVI. Ask your healthcare provider if you do not know if you have lived in an area where these infections are common.
- think you have an infection or have symptoms of an infection such as:
  - fever, sweating, or chills
  - shortness of breath
  - warm, red or painful skin or sores on your body
  - burning when you urinate or urinating more often than normal
  - muscle aches
  - blood in your phlegm
  - diarrhea or stomach pain
  - cough
  - weight loss
  - feeling very tired

After starting LEQSELVI, call your healthcare provider right away if you have any symptoms of an infection. LEQSELVI can make you more likely to get infections or make any infections that you have worse. If you get a serious infection, your healthcare provider may stop your treatment with LEQSELVI until your infection is controlled.

2. Increased risk of death in people 50 years of age and older who have at least 1 heart disease (cardiovascular) risk factor and are taking a medicine in the class of medicines called Janus kinase (JAK) inhibitors. LEQSELVI is a JAK inhibitor medicine.

3. Cancer and immune system problems. LEQSELVI may increase your risk of certain cancers by changing the way your immune system works.

- Lymphoma and other cancers, including skin cancers, can happen in people taking LEQSELVI. People taking a medicine in the class of medicines called Janus kinase (JAK) inhibitors have a higher risk of certain cancers including lymphoma and lung cancer, especially if you are a current or past smoker.
- Follow your healthcare provider’s advice about having your skin checked for skin cancer during treatment with LEQSELVI.

Tell your healthcare provider if you have ever had any type of cancer.

4. Increased risk of major cardiovascular events such as heart attack, stroke or death in people 50 years of age and older who have at least 1 heart disease (cardiovascular) risk factor and taking a medicine in the class of medicines called JAK inhibitors, especially if you are a current or past smoker.

Get emergency help right away if you get any symptoms of a heart attack or stroke during treatment with LEQSELVI, including:

- discomfort in the center of your chest that lasts for more than a few minutes, or that goes away and comes back
- severe tightness, pain, pressure, or heaviness in your chest, throat, neck, or jaw
- pain or discomfort in your arms, back, neck, jaw, or stomach
- shortness of breath with or without chest discomfort
- breaking out in a cold sweat
- nausea or vomiting
- feeling lightheaded
- weakness in one part or on one side of your body
- slurred speech

5. Blood clots. Blood clots in the veins of your legs (deep vein thrombosis, DVT), lungs (pulmonary embolism, PE) or brain (cerebral venous sinus thrombosis, CVT) can happen in some people during treatment with LEQSELVI. This may be life-threatening and may cause death. Blood clots in the veins of the legs (DVT) and lungs (PE) have happened more often in people who are 50 years of age and older and with at least 1 heart disease (cardiovascular) risk factor taking a medicine in the class of medicines called Janus kinase (JAK) inhibitors.

- Tell your healthcare provider if you have had blood clots in the veins of your legs, lungs, or brain in the past.
- Stop taking LEQSELVI and tell your healthcare provider or get medical help right away if you get any signs or symptoms of blood clots during treatment with LEQSELVI, including:
  - swelling, pain or tenderness in one or both legs
  - sudden, unexplained chest or upper back pain
  - shortness of breath or difficulty breathing
  - severe headaches

6. Tears (perforation) in the stomach or intestines.

- Tell your healthcare provider if you have had diverticulitis (inflammation in parts of the large intestine) or ulcers in your stomach or intestines. Some people taking LEQSELVI can get tears in their stomach or intestines.
- Call your healthcare provider or go to the nearest hospital emergency room right away if you have stomach-area pain, fever, chills, nausea or vomiting.

7. Changes in certain laboratory test results. Your healthcare provider should do blood tests before you start taking LEQSELVI and during treatment to check for the following:

- increased fat (lipid) levels in your blood (triglycerides and cholesterol).
- low red blood cell counts. This may mean that you have anemia, which may make you feel weak or tired.
- low lymphocyte or neutrophil counts. Lymphocytes and neutrophils are white blood cells that help the body fight off infections.

You should not take LEQSELVI if your white blood cell or red blood cell counts are too low. Your healthcare provider may stop your LEQSELVI treatment for period of time if needed because of changes in these blood test results.

See “What are the possible side effects of LEQSELVI?” for more information about side effects.

What is LEQSELVI?
LEQSELVI is a prescription medicine that is a Janus Kinase (JAK) inhibitor. LEQSELVI is used to treat adults with severe hair loss (alopecia areata).
It is not known if LEQSELVI is safe and effective in children.

Do not take LEQSELVI if you:

- are a poor metabolizer of CYP2C9 medicines. Before starting treatment with LEQSELVI, your healthcare provider should test you for CYP2C9 variants.
- take moderate or strong CYP2C9 inhibitor medicines. Ask your healthcare provider or pharmacist if you are not sure if you take any of these medicines.

Before taking LEQSELVI, tell your healthcare provider about all of your medical conditions, including if you:

- See “What is the most important information I should know about LEQSELVI?”
- have an infection.
- are a current or past smoker.
- have had a heart attack, or other heart problems or stroke.
- have had blood clots in your legs, lungs or brain.
- have kidney problems.
- have liver problems.
- have any stomach area (abdominal) pain or been diagnosed with diverticulitis or ulcers in your stomach or intestine.
- have low red or white blood cell counts.
- have recently received or are scheduled to receive a vaccine. People who take LEQSELVI should not receive live vaccines.
- are pregnant or plan to become pregnant. It is not known if LEQSELVI will harm an unborn baby. Tell your healthcare provider if you are pregnant or plan to become pregnant during treatment with LEQSELVI.
  - Females who are able to become pregnant should use effective birth control (contraception) during treatment with LEQSELVI. Talk to your healthcare provider about birth control methods that may be right for you during treatment with LEQSELVI.
  - If you become pregnant during treatment with LEQSELVI, call Sun Pharmaceuticals Industries, Inc at 1-800- 818-4555 to report your pregnancy.
- are breastfeeding or plan to breastfeed. It is not known if LEQSELVI passes into your breastmilk. You should not breastfeed during treatment with LEQSELVI and for 1 day after the last dose. Talk to your healthcare provider about the best way to feed your baby during treatment with LEQSELVI.

Tell your healthcare provider about all the medicines you take, including prescription and over-the-counter medicines, vitamins, and herbal supplements. LEQSELVI and other medicines may affect each other causing side effects.

Especially tell your healthcare provider if you take medicines that affect your immune system such as biologic medicines, other JAK inhibitors, and strong immunosuppressants (such as cyclosporine) as these medicines may increase your risk of infection.

Ask your healthcare provider or pharmacist if you are not sure if you are taking one of these medicines. Know the medicines you take. Keep a list of them to show your healthcare provider and pharmacist whenever you get a new medicine.

How should I take LEQSELVI?

- Take LEQSELVI exactly as your healthcare provider tells you to take it.
- Take LEQSELVI 2 times a day with or without food.
- If you miss a dose of LEQSELVI, skip the missed dose and take the next dose at your regularly scheduled time.
- If you take too much LEQSELVI, call your healthcare provider or poison control center at 1-800-222-1222, or go to the nearest hospital emergency room right away.

What are the possible side effects of LEQSELVI?
LEQSELVI may cause serious side effects, including:

- See “What is the most important information I should know about LEQSELVI?”

The most common side effects of LEQSELVI include:

- headache
- acne
- pain or swelling of your nose or throat (nasopharyngitis)
- increased blood creatine phosphokinase
- increased blood cholesterol
- tiredness
- weight gain
- increased platelets in your blood (thrombocytosis)
- low red blood cell count (anemia)
- skin and soft tissue infections
- low white blood cell count (neutropenia)
- herpes simplex including cold sores

These are not all of the possible side effects of LEQSELVI.

Call your doctor for medical advice about side effects. You may report side effects to FDA at 1-800-FDA-1088.

How should I store LEQSELVI?

- Store LEQSELVI at room temperature between 68°F to 77°F (20°C to 25°C).
- Store LEQSELVI in the original container to protect from moisture.
- LEQSELVI comes with a child-resistant cap.

Keep LEQSELVI and all medicines out of the reach of children.

General information about the safe and effective use of LEQSELVI.

Medicines are sometimes prescribed for purposes other than those listed in a Medication Guide. Do not use LEQSELVI for a condition for which it was not prescribed. Do not give LEQSELVI to other people, even if they have the same symptoms that you have. It may harm them. You can ask your pharmacist or healthcare provider for information about LEQSELVI that is written for health professionals.

What are the ingredients in LEQELVI?

Active ingredient: deuruxolitinib

Inactive ingredients: colloidal silicon dioxide, lactose monohydrate, low-substituted hydroxypropyl cellulose, magnesium stearate, microcrystalline cellulose and povidone. The tablet film coat contains: carmine, FD&C blue #2 aluminum lake, glyceryl mono and dicaprylocaprate, polyvinyl alcohol, sodium lauryl sulfate, talc, and titanium dioxide.

Manufactured for Sun Pharmaceutical Industries, Inc. by Halo Pharmaceutical Inc., Whippany, NJ, 07981, USA.

This Medication Guide has been approved by the U.S. Food and Drug Administration.

Issued: 7/2024